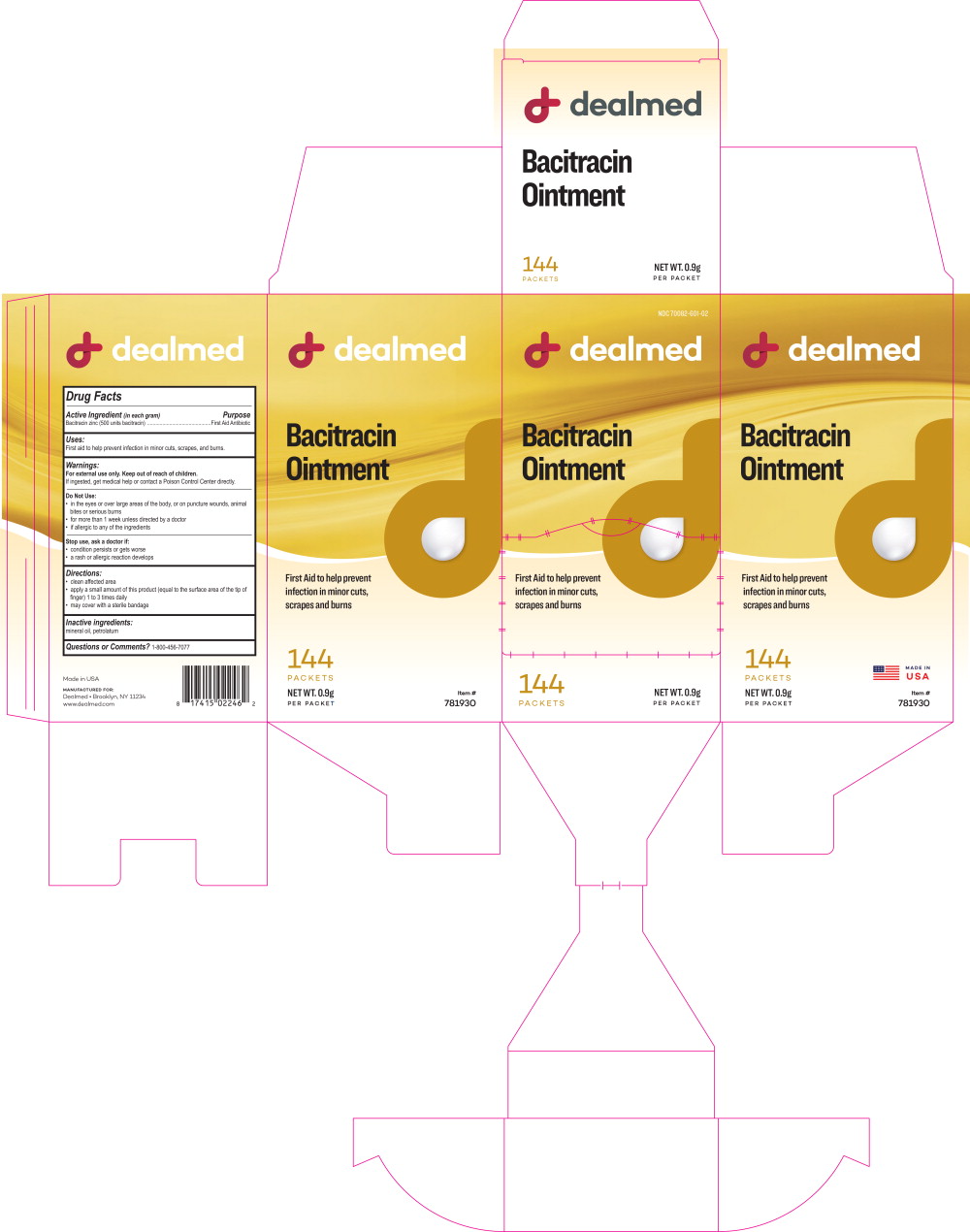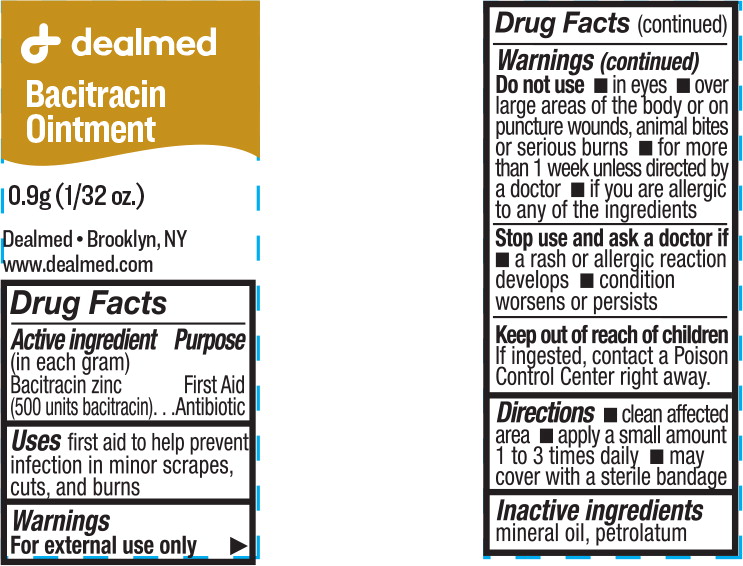 DRUG LABEL: Single Antibiotic with bacitracin
NDC: 70082-601 | Form: OINTMENT
Manufacturer: Dealmed Medical Supplies LLC
Category: otc | Type: HUMAN OTC DRUG LABEL
Date: 20220308

ACTIVE INGREDIENTS: bacitracin zinc 400 [USP'U]/1 g
INACTIVE INGREDIENTS: petrolatum

Drug Facts

Active Ingredient (in each gram)

Bacitracin zinc (500 units bacitracin)

Purpose

First Aid Antibiotic

Uses:

First aid to help prevent infection in minor cuts, scrapes, and burns.

Warnings:

For external use only.

Keep out of reach of children.

If ingested, get medical help or contact a Poison Control Center directly.

Do Not Use:

- in the eyes or over large areas of the body, or on puncture wounds, animal bites or serious burns
- for more than 1 week unless directed by a doctor
- if allergic to any of the ingredients

Stop use, ask a doctor if:

- condition persists or gets worse
- a rash or allergic reaction develops

Directions:

- clean affected area
- apply a small amount of this product (equal to the surface area of the tip of finger) 1 to 3 times daily
- may cover with a sterile bandage

Inactive ingredients:

mineral oil, petrolatum

Questions or Comments?

1-800-456-7077

Principal Display Panel - 0.9g Box Label

NDC 70082-601-02

dealmed

Bacitracin
Ointment

First Aid to help prevent
infection in minor cuts,
scrapes and burns

144
Packets

NET WT. 0.9g
PER PACKET

Principal Display Panel - 0.9g Pouch Label

dealmed

Bacitracin
Ointment

0.9g (1/32 oz.)

Dealmed • Brooklyn, NY

www.dealmed.com